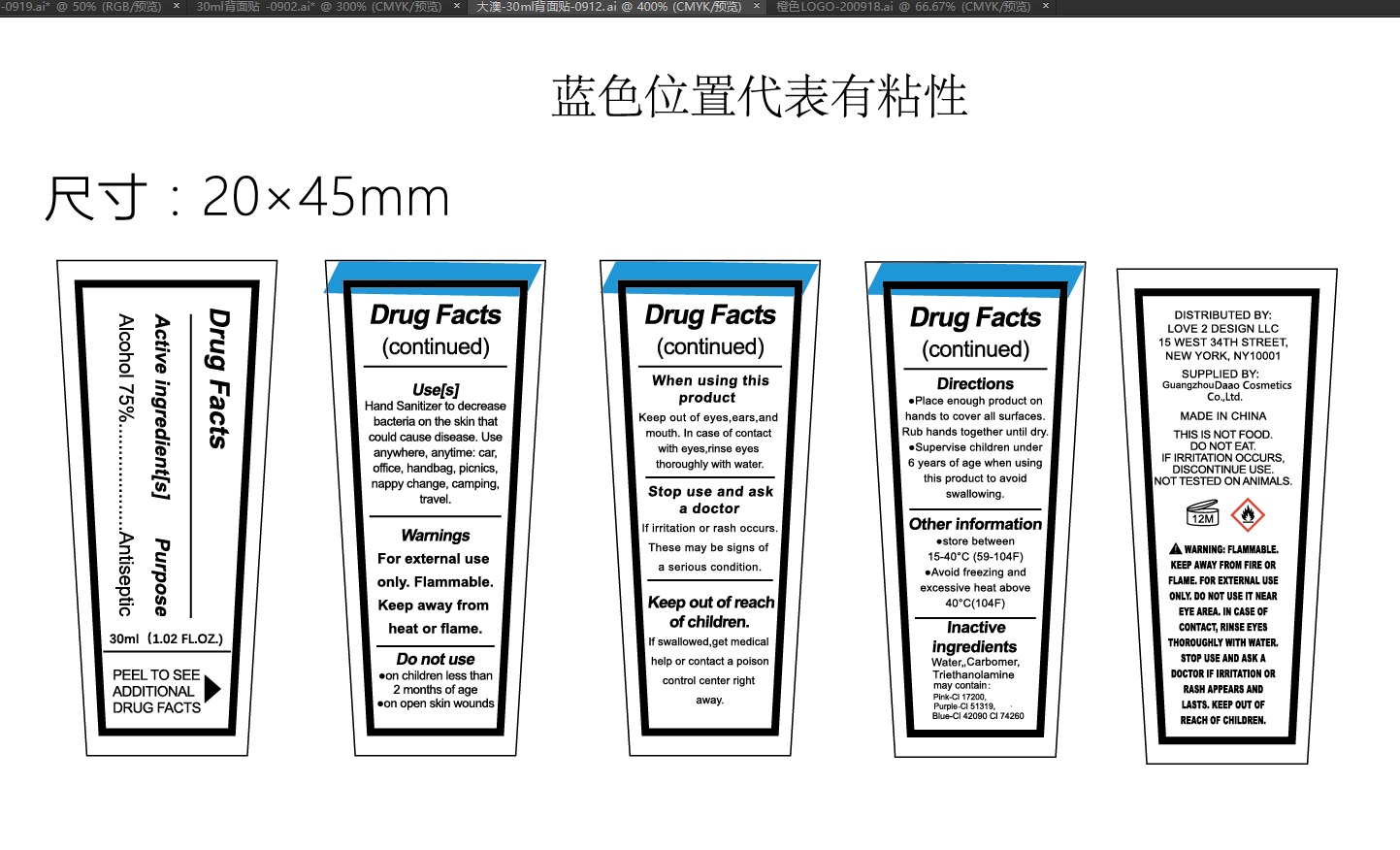 DRUG LABEL: Hand Sanitizer
NDC: 52965-010 | Form: GEL
Manufacturer: Guangzhou Da'ao Cosmetics Co., Ltd
Category: otc | Type: HUMAN OTC DRUG LABEL
Date: 20200923

ACTIVE INGREDIENTS: ALCOHOL 22.5 mL/30 mL
INACTIVE INGREDIENTS: FD&C BLUE NO. 1; D&C RED NO. 33; TROLAMINE; WATER; CARBOMER HOMOPOLYMER, UNSPECIFIED TYPE; PIGMENT VIOLET 23; PIGMENT GREEN 7

DOSAGE AND ADMINISTRATION

●store between 15- 40°C (59-104°F)
●Avoid freezing and excessive heat above 40°C(104°F)

INACTIVE INGREDIENT

WATER,CARBOMER,TRIETHANOLAMINE,CI 17200,CI 51319,CI 42090,CI 74260

INDICATIONS AND USAGE

Place enough product on hands to cover all surfaces.Rub hands together until dry.

ACTIVE INGREDIENT

ALCOHOL

PURPOSE

Disinfe ction
Sterilization
No Rinseing

keep out of reach of children,If swallowed,get medicalhelp or contact a poison control center right away.

WARNINGS

For external use only. Flammable.Keep away from heat or flame.